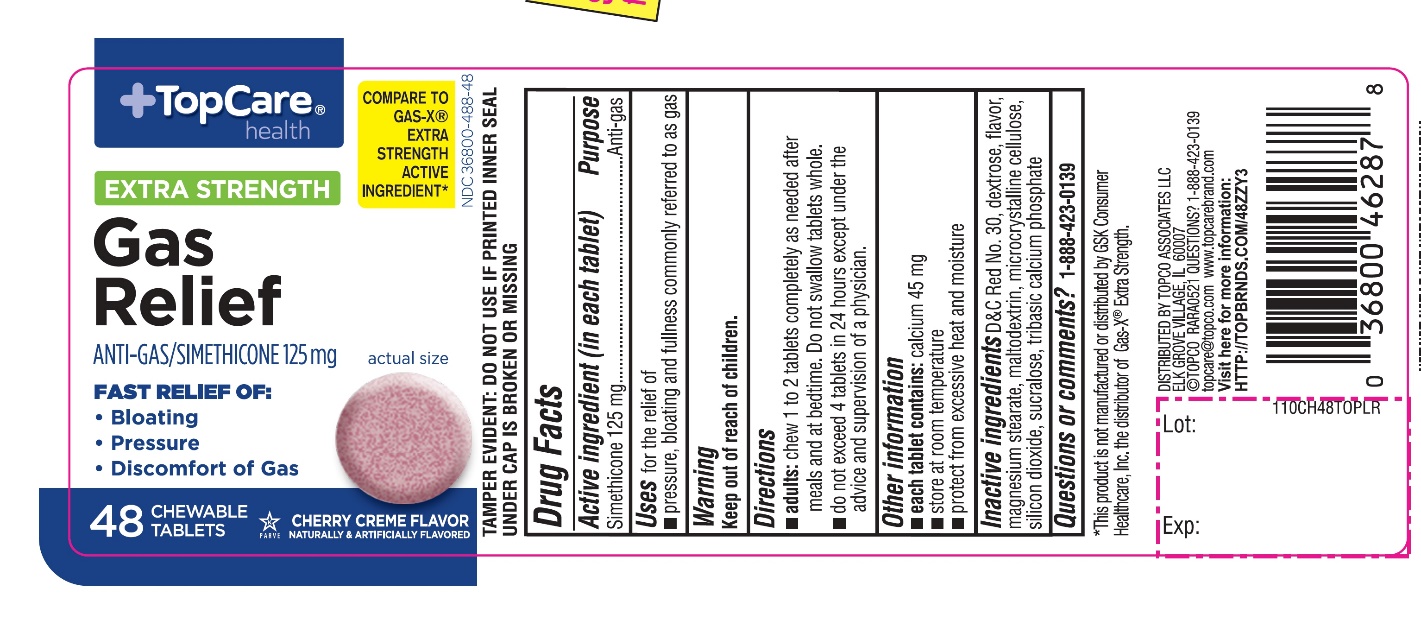 DRUG LABEL: TopCare Extra Strength Gas Relief

NDC: 36800-488 | Form: TABLET, CHEWABLE
Manufacturer: TOPCO ASSOCIATES LLC
Category: otc | Type: HUMAN OTC DRUG LABEL
Date: 20251110

ACTIVE INGREDIENTS: DIMETHICONE, UNSPECIFIED 125 mg/1 1
INACTIVE INGREDIENTS: D&C RED NO. 30; DEXTROSE, UNSPECIFIED FORM; MAGNESIUM STEARATE; MALTODEXTRIN; MICROCRYSTALLINE CELLULOSE; SILICON DIOXIDE; SUCRALOSE; TRIBASIC CALCIUM PHOSPHATE

TopCare® Extra Strength Gas Relief 48 Chewable Tablets

Active ingredient (in each tablet)

Simethicone 125 mg

Purpose

Anti-gas

Uses

Foe the relief of

- pressure, bloating and fullness commonly referred to as gas

Directions

- adults:chew 1 to 2 tablets as needed after meals and at bedtime
- do not exceed 4 tablets in 24 hour except under the advice and supervision of a physician

Other information

- each tablet contains:calcium 45 mg
- store at room temperature
- protect from excessive heat and moisture

Inactive ingredients

D&C Red No. 30, dextrose, flavor, magnesium stearate, maltodextrin, microcrystalline cellulose, silica, sucralose, tribasic calcium phosphate

Questions or comments?

1-866-467-2748

Principal Display Panel

NDC 36800-488-48

COMPARE TO GAS-X®E XTRA STRENGTH ACTIVE INGREDIENT*

EXTRA STRENGTH

Gas Relief

ANTIGAS/SIMETHICONE 125 mg

- FOR FAST RELIEF OF

- Bloating
- Pressure
- Discomfort of Gas

CHERRY CREME FLAVOR

Naturally and Artificially Flavored

48 CHEWABLE TABLETS

DO NOT USE IF PRINTED INNER SEAL IS BROKEN OR MISSING

DISTRIBUTED BY: TOPCO ASSOCIATES LLC,

ELK GROVE VILLAGE, IL 60007

© TOPCO RARA1217

QUESTIONS? 1-888-423-0139

topcare@topco.com, www.topcarebrand.com

*This product is not manufactured or distributed by GSK Consumer Healthcare, Inc., the distributor of GAS-X® Extra Strength.